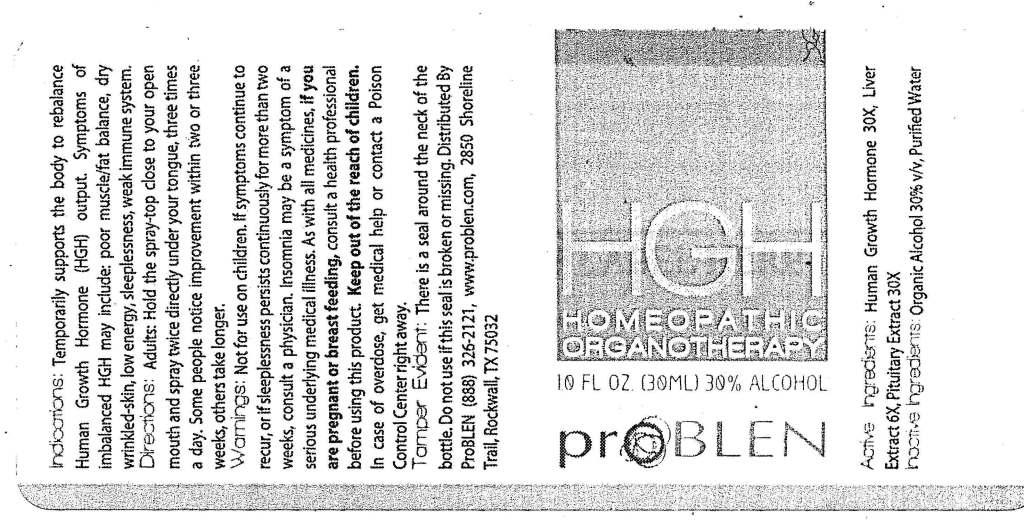 DRUG LABEL: ProBlen HGH
NDC: 50845-0015 | Form: SPRAY
Manufacturer: Liddell Laboratories, Inc.
Category: homeopathic | Type: HUMAN OTC DRUG LABEL
Date: 20120206

ACTIVE INGREDIENTS: SOMATROPIN 30 [hp_X]/1 mL; BEEF LIVER 6 [hp_X]/1 mL; BOS TAURUS PITUITARY GLAND 30 [hp_X]/1 mL
INACTIVE INGREDIENTS: WATER; ALCOHOL

ProBLEN HGH

ACTIVE INGREDIENT

ACTIVE INGREDIENTS: Human growth hormone 30X, Hepar bovinum 6X, Pituitary bovinum 30X.

PURPOSE

INDICATIONS: Temporarily supports the body to rebalance Human Growth Hormone (HGH) output. Symptoms of imbalanced HGH may include: poor muscle/fat balance, dry wrinkled-skin, low energy, sleeplessness, weak immune system.

WARNINGS: Not for use on children.

If symptoms continue to recur, or if sleeplessness persists continuously for more than two weeks, consult a physician. Insomnia may be a symptom of a serious underlying medical illness.

As with all medicines, if you are pregnant or breast feeding, consult a health professional before using this product.

Keep out of reach of children. In case of overdose, get medical help or contact a Poison Control Center right away.

TAMPER EVIDENT: There is a seal around the neck of the bottle. Do not use if this seal is broken or missing.

DOSAGE AND ADMINISTRATION

DIRECTIONS: Adults: Hold the spray top close to your open mouth and spray twice directly under your tongue, three times a day. Some people notice improvement within two or three weeks, others take longer.

INACTIVE INGREDIENT

INACTIVE INGREDIENTS: Organic alcohol 30% v/v, Purified water.

KEEP OUT OF REACH OF CHILDREN. In case of overdose, get medical help or contact a Poison Control Center right away.

INDICATIONS AND USAGE

INDICATIONS: Temporarily supports the body to rebalance Human Growth Hormone (HGH) output. Symptoms of imbalanced HGH may include: poor muscle/fat balance, dry wrinkled skin, low energy, sleeplessness, weak immune system.

QUESTIONS

Distributed by:

ProBLEN

(888) 326-2121

www.problen.com

2850 Shoreline Trail

Rockwall, TX 75032

PACKAGE LABEL

HGH

HOMEOPATHIC ORGANOTHERAPY

1.0 FL OZ (30 ML)

proBLEN